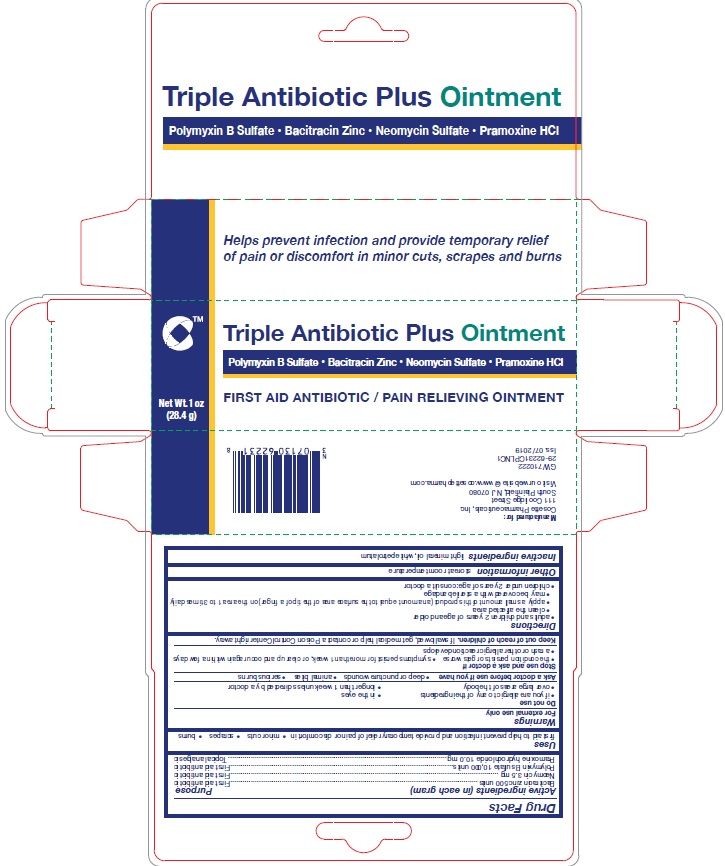 DRUG LABEL: Triple Antibiotic Plus 
NDC: 0713-0622 | Form: OINTMENT
Manufacturer: Cosette Pharmaceuticals, Inc.
Category: otc | Type: HUMAN OTC DRUG LABEL
Date: 20231221

ACTIVE INGREDIENTS: Polymyxin B Sulfate 10000 [USP'U]/1 g; Bacitracin Zinc 500 [USP'U]/1 g; Neomycin 3.5 mg/1 g; Pramoxine Hydrochloride 10 mg/1 g
INACTIVE INGREDIENTS: Light Mineral Oil; Petrolatum

Triple Antibiotic Plus Ointment
Polymyxin B Sulfate • Bacitracin Zinc • Neomycin Sulfate • Pramoxine HCl

ACTIVE INGREDIENT

Active ingredients (in each gram) | Purpose
Bacitracin zinc 500 units | First aid antibiotic
Neomycin 3.5 mg | First aid antibiotic
Polymyxin B sulfate 10,000 units | First aid antibiotic
Pramoxine hydrochloride 10.0 mg | Topical analgesic

USES

first aid to help prevent infection and provide temporary relief of pain or discomfort in minor • cuts • scrapes • burns

WARNINGS

For external use only.
Do not use

- if you are allergic to any of the ingredients
- in the eyes
- over large areas of the body
- longer than 1 week unless directed by a doctor.

Ask a doctor before use if you have

- deep or puncture wounds
- animal bites
- serious burns

Stop use and ask a doctor if

- the condition persists or gets worse
- symptoms persist for more than 1 week, or clear up and occur again within a few days
- a rash or other allergic reaction develops

KEEP OUT OF REACH OF CHILDREN

If swallowed, get medical help or contact a Poison Control Center right away.

DIRECTIONS

• adults and children 2 years of age and older
• clean the affected area
• apply a small amount of this product (an amount equal to the surface area of the tip of a finger) on the area 1 to
3 times daily
• may be covered with a sterile bandage
• children under 2 years of age: consult a doctor

OTHER INFORMATION

store at room temperature

INACTIVE INGREDIENT

light mineral oil, white petrolatum

PRINCIPAL DISPLAY PANEL

Triple Antibiotic Plus Ointment
Polymyxin B Sulfate • Bacitracin Zinc • Neomycin Sulfate • Pramoxine HCl
FIRST AID ANTIBIOTIC / PAIN RELIEVING OINTMENT
Net Wt. 1 oz
(28.4 g)